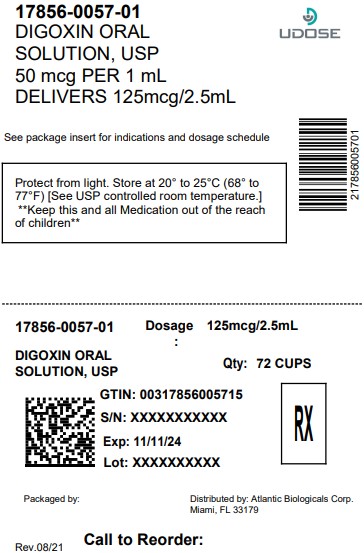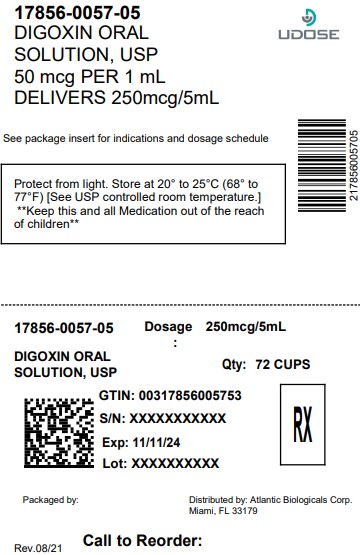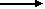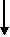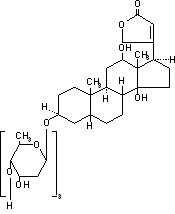 DRUG LABEL: Digoxin
NDC: 17856-0057 | Form: SOLUTION
Manufacturer: Atlantic Biologicals Corps
Category: prescription | Type: HUMAN PRESCRIPTION DRUG LABEL
Date: 20251211

ACTIVE INGREDIENTS: DIGOXIN 0.05 mg/1 mL
INACTIVE INGREDIENTS: ALCOHOL; GLYCERIN; LIME (CITRUS); METHYLPARABEN; PROPYLPARABEN; SODIUM CITRATE; SORBITOL; WATER

HIGHLIGHTS OF PRESCRIBING INFORMATION

Digoxin Oral Solution
These highlights do not include all the information needed to use Digoxin Oral Solution safely and effectively. See full prescribing information for Digoxin Oral Solution. Initial U.S. Approval: 1982

1 INDICATIONS AND USAGE

In adults, digoxin is indicated for the treatment of mild to moderate heart failure and for the control of resting ventricular rate in patients with chronic atrial fibrillation. (1) In pediatric patients with heart failure, digoxin increases myocardial contractility.

2 DOSAGE AND ADMINISTRATION

Toxic levels of digoxin are only slightly higher than therapeutic levels. The pharmacokinetics of digoxin are complex and dose determination should take into account patient-specific factors (age, lean body weight, renal function, etc.). (2.4)(2.5) Patients should be monitored for toxicity and therapeutic effect and doses should be adjusted, accordingly. (2.2)

3 DOSAGE FORMS AND STRENGTHS

Oral Solution: Each 1 mL contains 0.05 mg (50 mcg) of digoxin. (3)

4 CONTRAINDICATIONS

- Known hypersensitivity to digoxin or other forms of digitalis. (4)
- Ventricular fibrillation. (4)

5 WARNINGS AND PRECAUTIONS

- Accessory AV Pathway: Increased risk of rapid ventricular response leading to ventricular fibrillation. (5.1)
- Sinus node disease and AV block: Digoxin use can exacerbate the condition and may cause advanced or complete heart block. (5.2)
- Misidentification of digoxin toxicity: Signs and symptoms of digoxin toxicity may be mistaken for worsening symptoms of congestive heart failure. (5.3)
- Preserved left ventricular systolic function: Patients with heart failure with preserved left ventricular ejection fraction may be more susceptible to digoxin toxicity. (5.4)
- Impaired renal function: Renal impairment results in increased digoxin exposure and requires dosage adjustments. (5.5)
- Electrolyte disorders: Toxicity is increased by hypokalemia, hypomagnesemia, and hypercalcemia. (5.6)
- Hypermetabolic states: In patients with atrial arrhythmias associated with hypermetabolic states, control of resting ventricular rate is particularly resistant to digoxin treatment. (5.8)
- The use of digoxin may result in potentially detrimental increases in coronary vascular resistance. (5.9)
- Avoid digoxin in patients with myocarditis. (5.10)

6 ADVERSE REACTIONS

The overall incidence of adverse reactions with digoxin has been reported as 5 to 20%, with 15 to 20% of adverse events considered serious. Cardiac toxicity accounts for about one-half, gastrointestinal disturbances for about one-fourth, and CNS and other toxicity for about one-fourth of these adverse events. (6)

To report SUSPECTED ADVERSE REACTIONS, contact Roxane Laboratories, Inc. at (614) 962-8364 or FDA at 1-800-FDA-1088 or www.fda.gov/medwatch

7 DRUG INTERACTIONS

- PGP Inducers/Inhibitors: Drugs that induce or inhibit PGP have the potential to alter digoxin pharmacokinetics. (7.1)
- There are numerous drug interactions associated with digoxin. The potential for drug-drug interactions must be considered prior to and during drug therapy. See full prescribing information for a complete listing of pharmacokinetic (7.2) (12.3) and pharmacodynamic interactions (7.3).

8 USE IN SPECIFIC POPULATIONS

- Geriatric patients (8.5): Use caution during dose selection, taking into account renal function, and carefully monitor for side effects.
- Renal impairment (8.7): Digoxin is excreted by the kidneys. Renal function should be considered during dosage selection.
- Pregnant patients (8.1): Digoxin is classified as Pregnancy Category C, it is unknown whether use during pregnancy can cause fetal harm.

FULL PRESCRIBING INFORMATION

1 INDICATIONS AND USAGE

1.1 Heart Failure

Digoxin Oral Solution, USP is indicated for the treatment of mild to moderate heart failure. Digoxin increases left ventricular ejection fraction and improves heart failure symptoms as evidenced by increased exercise capacity and decreased heart failure-related hospitalizations and emergency care, while having no effect on mortality. Where possible, digoxin should be used with a diuretic and an angiotensin-converting enzyme inhibitor, but an optimal order for starting these three drugs cannot be specified.

1.2 Heart Failure in Pediatric Patients

Digoxin increases myocardial contractility in pediatric patients with heart failure.

1.3 Atrial Fibrillation in Adults

Digoxin Oral Solution, USP is indicated for the control of resting ventricular response rate in patients with chronic atrial fibrillation. Digoxin should not be used for the treatment of multifocal atrial tachycardia.

2 DOSAGE AND ADMINISTRATION

2.1 General Dosing Considerations

The dose of digoxin should be based on clinical assessment but individual patient factors should be taken into consideration. Those factors are:

- Lean body weight
- Renal function
- Patient age
- Concurrent disease ] [see Warnings and Precautions (5)
- Concomitant medication [see ] Drug Interactions (7)

Because the pharmacokinetics of digoxin are complex, and because toxic levels of digoxin are only slightly higher than therapeutic levels, digoxin dosing can be difficult. The recommended approach is to

- estimate the patient’s daily maintenance dose
- adjust the estimate to account for patient-specific factors
- choose a dosing regimen
- decide whether to initiate therapy with a loading dose
- monitor the patient for toxicity and for therapeutic effect
- adjust the dose

Dose titration may be accomplished by either of two general approaches that differ in dosage and frequency of administration, but reach the same total amount of digoxin accumulated in the body.

1. If rapid titration is considered medically appropriate, administer a loading dose based upon projected peak digoxin body stores. Maintenance dose can be calculated as a percentage of the loading dose.
2. More gradual titration may be obtained by beginning an appropriate maintenance dose, thus allowing digoxin body stores to accumulate slowly. Steady-state serum digoxin concentrations will be achieved in approximately five half-lives of the drug for the individual patient. Depending upon the patient’s renal function, this will take between 1 and 3 weeks.

2.2 Serum Digoxin Concentrations

In general, the dose of digoxin used should be determined on clinical grounds. However, measurement of serum digoxin concentrations can be helpful to the clinician in determining the adequacy of digoxin therapy and in assigning certain probabilities to the likelihood of digoxin intoxication.

Studies have shown diminished efficacy at serum levels < 0.5 ng/mL, while levels above 2 ng/mL are associated with increased toxicity without increased benefit. The inotropic effects of digoxin tend to appear at lower concentrations than the electrophysiological effects. Based on retrospective analysis, adverse events may be higher in the upper therapeutic range.

Perform sampling of serum concentrations just before the next scheduled dose of the drug. If this is not possible, sample at least 6 hours or later after the last dose, regardless of the route of administration or the formulation used. On a once-daily dosing schedule, the concentration of digoxin will be 10% to 25% lower when sampled at 24 versus 8 hours, depending upon the patient’s renal function. On a twice-daily dosing schedule, there will be only minor differences in serum digoxin concentrations whether sampling is done at 8 or 12 hours after a dose. The serum concentration of digoxin should always be interpreted in the overall clinical context, and an isolated measurement should not be used alone as the basis for increasing or decreasing the dose of the drug.

When decision-making is to be guided by serum digoxin levels, the clinician must consider the possibility of reported concentrations that have been falsely elevated by endogenous digoxin-like immunoreactive substances If the assay being used is sensitive to these substances, it may be prudent to obtain a baseline measurement before digoxin therapy is started, and correct later values by the reported baseline level. [see ] Drug Interactions (7.4).

2.3 Loading Dose

Loading doses for each age group are given in Table 1 below.

In pediatric patients, if a loading dose is needed, it can be administered with roughly half the total given as the first dose. Additional fractions of this planned total dose may be given at 4- to 8-hour intervals, with careful assessment of clinical response before each additional dose. If the patient’s clinical response necessitates a change from the calculated loading dose of digoxin, then calculation of the maintenance dose should be based upon the amount actually given as the loading dose [see and ]. Table 12

Table 1: Estimate the Loading Dose
Age | Oral Loading Dose, mcg/kg
Premature | 20 - 30
Full-Term | 25 - 35
1 to 24 months | 35 - 60
2 to 5 years | 30 - 45
5 to 10 years | 20 - 35
Over 10 years | 10 - 15

More gradual attainment of digoxin levels can also be accomplished by beginning an appropriate maintenance dose. The range of percentages provided in Table 2 (2.4 Estimate of Daily Maintenance Dose) can be used in calculating this dose for patients with normal renal function. Steady state will be attained after approximately 5 days in subjects with normal renal function.

2.4 Estimate of Daily Maintenance Dose

The recommended daily maintenance doses for each age group are given in Table 2 below. These recommendations assume the presence of normal renal function.

Table 2: Estimate of the Daily Maintenance Dose
Age | Daily Oral Maintenance Dose, mcg/kg/day | Dose Regimen, mcg/kg/dose
Premature | 4.7 – 7.8 | 2.3 – 3.9 Twice daily
Full-Term | 7.5 – 11.3 | 3.8 – 5.6 Twice daily
1 to 24 months | 11.3 – 18.8 | 5.6 – 9.4 Twice daily
2 to 5 years | 9.4 – 13.1 | 4.7 – 6.6 Twice daily
5 to 10 years | 5.6 – 11.3 | 2.8 – 5.6 Twice daily
Over 10 years | 3.0 – 4.5 | 3.0 – 4.5 Once daily

Dosage guidelines provided are based upon average patient response and substantial individual variation can be expected. Accordingly, dosage selection must be based upon clinical assessment and ultimately therapeutic drug level monitoring of the patient.

Divided daily dosing is recommended for pediatric patients under age 10. In the newborn period, renal clearance of digoxin is diminished and suitable dosage adjustments must be made as shown in Tables 1 and 2. Renal clearance is further reduced in the premature infant. Beyond the immediate newborn period, pediatric patients generally require proportionally larger doses than adults on the basis of body weight or body surface area. Pediatric patients over 10 years of age require adult dosages in proportion to their body weight. Some researchers have suggested that infants and young pediatric patients tolerate slightly higher serum concentrations than do adults. For pediatric patients with known or suspected renal dysfunction, lower starting doses should be considered combined with frequent monitoring of digoxin levels.

The calibrated dropper supplied with the 60 mL bottle of digoxin oral solution is not appropriate to measure doses below 0.2 mL. Doses less than 0.2 mL require appropriate methods or measuring devices designed to administer an accurate amount to the patient, such as a graduated syringe. NOTE:

2.5 Adjustment of Dose

The body’s handling of digoxin can be affected by many different patient-specific factors. Some of the possible effects are small, so anticipatory dose adjustment might not be required, but others should be considered before initial dosing . [see and Clinical Pharmacology (12.2)] Drug Interactions (7)

Both adults and pediatric patients with abnormal renal function need to have the dose of digoxin proportionally reduced. Recommended maintenance doses based upon lean body weight and renal function are listed in . Developmental changes in pediatric renal function were factored into Table 3. However, age-related and other changes in adult renal function were not. Table 3

The volume of distribution of digoxin is proportional to lean body weight and doses listed in Table 3 assume average body composition. The dose of digoxin must be reduced in patients whose lean weight is an abnormally small fraction of their total body mass because of obesity or edema.

Table 3: Usual Maintenance Dose Requirements (mcg) of Digoxin Based upon Age, Lean Body Weight and Renal Function
Corrected Ccr; (mL/min per 70 kg) [Ccr is creatinine clearance, corrected to 70 kg body weight or 1.73 m body surface area. , if only serum creatinine concentrations (Scr) are available, a Ccr (corrected to 70 kg body weight) may be estimated in men as (140 – Age)/Scr. For women, this result should be multiplied by 0.85. 2Foradults] |  | Dose to be given [The doses are rounded to whole numbers.] Twice Daily [Twice daily dosing is recommended for pediatric patients under 10 years of age. Once daily dosing is recommended for pediatric patients above 10 years of age and adults.] |  |  |  |  |  |  | Dose to be given Once Daily |  |  |  |  |  |  | Number of Days Before Steady State Achieve
Corrected Ccr; (mL/min per 70 kg) [Ccr is creatinine clearance, corrected to 70 kg body weight or 1.73 m body surface area. , if only serum creatinine concentrations (Scr) are available, a Ccr (corrected to 70 kg body weight) may be estimated in men as (140 – Age)/Scr. For women, this result should be multiplied by 0.85. 2Foradults] |  | < 10 years of age |  |  |  |  |  |  | > 10 years of age and adults |  |  |  |  |  |  | Number of Days Before Steady State Achieve
Corrected Ccr; (mL/min per 70 kg) [Ccr is creatinine clearance, corrected to 70 kg body weight or 1.73 m body surface area. , if only serum creatinine concentrations (Scr) are available, a Ccr (corrected to 70 kg body weight) may be estimated in men as (140 – Age)/Scr. For women, this result should be multiplied by 0.85. 2Foradults] |  | Lean Body Weight |  |  |  |  |  |  | Lean Body Weight |  |  |  |  |  |  | Number of Days Before Steady State Achieve
Corrected Ccr; (mL/min per 70 kg) [Ccr is creatinine clearance, corrected to 70 kg body weight or 1.73 m body surface area. , if only serum creatinine concentrations (Scr) are available, a Ccr (corrected to 70 kg body weight) may be estimated in men as (140 – Age)/Scr. For women, this result should be multiplied by 0.85. 2Foradults] | kg | 5 | 10 | 20 | 30 | 40 | 50 | 60 | 40 | 50 | 60 | 70 | 80 | 90 | 100 | Number of Days Before Steady State Achieve
Corrected Ccr; (mL/min per 70 kg) [Ccr is creatinine clearance, corrected to 70 kg body weight or 1.73 m body surface area. , if only serum creatinine concentrations (Scr) are available, a Ccr (corrected to 70 kg body weight) may be estimated in men as (140 – Age)/Scr. For women, this result should be multiplied by 0.85. 2Foradults] | lb | 11 | 22 | 44 | 66 | 88 | 110 | 132 | 88 | 110 | 132 | 154 | 176 | 198 | 220 | Number of Days Before Steady State Achieve
10 |  | 10 | 20 | 40 | 60 | 80 | 100 | 120 | 80 | 100 | 120 | 140 | 160 | 180 | 200 | 19
20 |  | 11 | 23 | 45 | 68 | 90 | 113 | 135 | 90 | 113 | 135 | 158 | 180 | 203 | 225 | 16
30 |  | 13 | 25 | 50 | 75 | 100 | 125 | 150 | 100 | 125 | 150 | 175 | 200 | 225 | 250 | 14
40 |  | 14 | 28 | 55 | 83 | 110 | 138 | 165 | 110 | 138 | 165 | 193 | 220 | 248 | 275 | 13
50 |  | 15 | 30 | 60 | 90 | 120 | 150 | 180 | 120 | 150 | 180 | 210 | 240 | 270 | 300 | 12
60 |  | 16 | 33 | 65 | 98 | 130 | 163 | 195 | 130 | 163 | 195 | 228 | 260 | 293 | 325 | 11
70 |  | 18 | 35 | 70 | 105 | 140 | 175 | 210 | 140 | 175 | 210 | 245 | 280 | 315 | 350 | 10
80 |  | 19 | 38 | 75 | 113 | 150 | 188 | 225 | 150 | 188 | 225 | 263 | 300 | 338 | 375 | 9
90 |  | 20 | 40 | 80 | 120 | 160 | 200 | 240 | 160 | 200 | 240 | 280 | 320 | 360 | 400 | 8
100 |  | 21 | 43 | 85 | 128 | 170 | 213 | 255 | 170 | 213 | 255 | 298 | 340 | 383 | 425 | 7

Determination of the target dose in milliliters of Digoxin Oral Solution based on body weight is shown in . Provided is the volume required per dose, NOT per day. Table 4

Table 4: Dose in Milliliters
Target Dose in mcg/kg |  | Volume to be given in mL
Target Dose in mcg/kg |  | 2 | 3 | 4 | 5 | 6 | 8 | 10 | 12 | 14 | 16 | 18 | 20 | 30
Weight in kg | 2 | 0.08b | 0.12b | 0.16b | 0.2 | 0.2 | 0.3 | 0.4 | 0.5 | 0.6 | 0.6 | 0.7 | 0.8 | 1.2
Weight in kg | 3 | 0.12b | 0.18b | 0.2 | 0.3 | 0.4 | 0.5 | 0.6 | 0.7 | 0.8 | 1.0 | 1.1 | 1.2 | 1.8
Weight in kg | 4 | 0.16b | 0.2 | 0.3 | 0.4 | 0.5 | 0.6 | 0.8 | 1.0 | 1.1 | 1.3 | 1.4 | 1.6 | 2.4
Weight in kg | 5 | 0.2 | 0.3 | 0.4 | 0.5 | 0.6 | 0.8 | 1.0 | 1.2 | 1.4 | 1.6 | 1.8 | 2.0 | 3.0
Weight in kg | 6 | 0.2 | 0.4 | 0.5 | 0.6 | 0.7 | 1.0 | 1.2 | 1.4 | 1.7 | 1.9 | 2.2 | 2.4 | 3.6
Weight in kg | 7 | 0.3 | 0.4 | 0.6 | 0.7 | 0.8 | 1.1 | 1.4 | 1.7 | 2.0 | 2.2 | 2.5 | 2.8 | 4.2
Weight in kg | 8 | 0.3 | 0.5 | 0.6 | 0.8 | 1.0 | 1.3 | 1.6 | 1.9 | 2.2 | 2.6 | 2.9 | 3.2 | 4.8
Weight in kg | 9 | 0.4 | 0.5 | 0.7 | 0.9 | 1.1 | 1.4 | 1.8 | 2.2 | 2.5 | 2.9 | 3.2 | 3.6 | 5.4
Weight in kg | 10 | 0.4 | 0.6 | 0.8 | 1.0 | 1.2 | 1.6 | 2.0 | 2.4 | 2.8 | 3.2 | 3.6 | 4.0 | 6.0
Weight in kg | 11 | 0.4 | 0.7 | 0.9 | 1.1 | 1.3 | 1.8 | 2.2 | 2.6 | 3.1 | 3.5 | 4.0 | 4.4 | 6.6
Weight in kg | 12 | 0.5 | 0.7 | 1.0 | 1.2 | 1.4 | 1.9 | 2.4 | 2.9 | 3.4 | 3.8 | 4.3 | 4.8 | 7.2
Weight in kg | 13 | 0.5 | 0.8 | 1.0 | 1.3 | 1.6 | 2.1 | 2.6 | 3.1 | 3.6 | 4.2 | 4.7 | 5.2 | 7.8
Weight in kg | 14 | 0.6 | 0.8 | 1.1 | 1.4 | 1.7 | 2.2 | 2.8 | 3.4 | 3.9 | 4.5 | 5.0 | 5.6 | 8.4
Weight in kg | 15 | 0.6 | 0.9 | 1.2 | 1.5 | 1.8 | 2.4 | 3.0 | 3.6 | 4.2 | 4.8 | 5.4 | 6.0 | 9.0
Weight in kg | 20 | 0.8 | 1.2 | 1.6 | 2.0 | 2.4 | 3.2 | 4.0 | 4.8 | 5.6 | 6.4 | 7.2 | 8.0 | 12.0
Weight in kg | 30 | 1.2 | 1.8 | 2.4 | 3.0 | 3.6 | 4.8 | 6.0 | 7.2 | 8.4 | 9.6 | 10.8 | 12.0 | 18.0
Weight in kg | 40 | 1.6 | 2.4 | 3.2 | 4.0 | 4.8 | 6.4 | 8.0 | 9.6 | 11.2 | 12.8 | 14.4 | 16.0 | 24.0
Weight in kg | 50 | 2.0 | 3.0 | 4.0 | 5.0 | 6.0 | 8.0 | 10.0 | 12.0 | 14.0 | 16.0 | 18 | 20.0 | 30.0
Weight in kg | 60 | 2.4 | 3.6 | 4.8 | 6.0 | 7.2 | 9.6 | 12.0 | 14.4 | 16.8 | 19.2 | 21.6 | 24.0 | 36.0
Weight in kg | 70 | 2.8 | 4.2 | 5.6 | 7.0 | 8.4 | 11.2 | 14.0 | 16.8 | 19.6 | 22.4 | 25.2 | 28.0 | 42.0
Weight in kg | 80 | 3.2 | 4.8 | 6.4 | 8.0 | 9.6 | 12.8 | 16.0 | 19.2 | 22.4 | 25.6 | 28.8 | 32.0 | 48.0
Weight in kg | 90 | 3.6 | 5.4 | 7.2 | 9.0 | 10.8 | 14.4 | 18.0 | 21.6 | 25.2 | 28.8 | 32.4 | 36.0 | 54.0
Weight in kg | 100 | 4.0 | 6.0 | 8.0 | 10.0 | 12.0 | 16.0 | 20.0 | 24.0 | 28.0 | 32.0 | 36.0 | 40.0 | 60.0

Recommended dosing regimen for pediatric patients under 10 years of age is twice daily. Recommended dosing regimen for pediatric patients over 10 years of age and adults is once daily.a

Use calibrated dropper for measurement. In the case of required volume less than 0.2 mL, a separate device such as a graduated syringe is recommended for adequate measurement.b

On the left side of the chart, locate the patient’s weight in kilograms. At the top of the chart, identify which dose in mcg/kg will be used for this patient. The block on the chart at which the two rows (weight and target dose) intersect is the milliliter amount that should be given to the patient.

The monitoring described in Section 2.2 may suggest increases or decreases in digoxin doses. Additional monitoring, and in some cases anticipatory dose adjustment, may be indicated around the time of various changes to the patient including:

- normal development through childhood;
- concomitant drug use should be considered when adjusting the estimated digoxin dose ; [see] Drug Interactions (7)
- new co-administration of an antibiotic, especially if the patient had required high doses of digoxin in order to achieve modest serum concentrations, raising the suspicion that a substantial fraction of administered digoxin was being destroyed by colonic bacteria; and
- changes in renal function . [see above] Table 3: Usual Maintenance Dose Requirements (mcg) of Digoxin

3 DOSAGE FORMS AND STRENGTHS

Each 1 mL of clear, colorless Digoxin Oral Solution contains 0.05 mg (50 mcg).

The Digoxin Oral Solution bottles are to be used with the graduated droppers provided in the carton. Starting at 0.2 mL, this 1 mL dropper is marked in divisions of 0.1 mL, corresponding to 5 mcg or 0.005 mg of digoxin.

The calibrated dropper supplied with the 60 mL bottle of Digoxin Oral Solution is not appropriate to measure doses below 0.2 mL. Doses less than 0.2 mL require appropriate methods or measuring devices designed to administer an accurate amount to the patient, such as a graduated syringe. NOTE:

4 CONTRAINDICATIONS

Allergy to digoxin is rare. Digoxin is contraindicated in patients with a known hypersensitivity to digoxin or other forms of digitalis. Digitalis glycosides, such as digoxin, are contraindicated in ventricular fibrillation.

5 WARNINGS AND PRECAUTIONS

5.1 Use in Patients with Accessory AV Pathway (Wolff-Parkinson-White Syndrome)

Patients with Wolff-Parkinson-White syndrome who develop atrial fibrillation are at high risk of ventricular fibrillation. Treatment of these patients with digoxin leads to greater slowing of conduction in the atrioventricular node than in accessory pathways, and the risks of rapid ventricular response leading to ventricular fibrillation are thereby increased.

5.2 Use in Patients with Sinus Node Disease and AV Block

Because digoxin slows sinoatrial and AV conduction, the drug commonly prolongs the PR interval. Digoxin may cause severe sinus bradycardia or sinoatrial block particularly in patients with pre-existing sinus node disease and may cause advanced or complete heart block in patients with pre-existing incomplete AV block. In such patients consideration should be given to the insertion of a pacemaker before treatment with digoxin.

5.3 Misidentification of Digoxin Toxicity

Some signs and symptoms (anorexia, nausea, vomiting, and certain arrhythmias) can equally result from digoxin toxicity as from congestive heart failure. Misidentification of their etiology might lead the clinician to continue or increase digoxin dosing, when dosing should actually be suspended. When the etiology of these signs and symptoms is not obvious, measurement of serum digoxin levels may be helpful.

5.4 Use in Patients with Preserved Left Ventricular Systolic Function

Patients with certain disorders involving heart failure associated with preserved left ventricular ejection fraction may not benefit from digoxin treatment and may be particularly susceptible to adverse reactions when they are treated with digoxin.

In patients with hypertrophic cardiomyopathy (formerly called idiopathic hypertrophic subaortic stenosis), the positive inotropic effect of digoxin leads to an increased subvalvular outflow gradient and therefore, may compromise cardiac output. Digoxin is rarely beneficial in patients with this condition.

Chronic constrictive pericarditis is not generally associated with any inotropic defect, so heart failure of this etiology is unlikely to respond to treatment with digoxin. By slowing the resting heart rate, digoxin may actually decrease cardiac output in these patients.

Digoxin as an inotropic agent is of limited value in patients with restrictive cardiomyopathies, although it has been used for ventricular rate control in the subgroup of patients with atrial fibrillation. In addition, patients with amyloid heart disease may be more susceptible to toxicity from digoxin at therapeutic levels because of an increased binding of digoxin to extracellular amyloid fibrils.

5.5 Use in Patients with Impaired Renal Function

Digoxin is primarily excreted by the kidneys; therefore, patients with impaired renal function require smaller than usual maintenance doses of digoxin . Because of the prolonged elimination half-life, a longer period of time is required to achieve an initial or new steady-state serum concentration in patients with renal impairment than in patients with normal renal function. If appropriate care is not taken to reduce the dose of digoxin, such patients are at high risk for toxicity, and toxic effects will last longer in such patients than in patients with normal renal function. [see Dosage and Administration (2.4)

5.6 Use During Electrical Cardioversion

In patients with hypokalemia or hypomagnesemia, toxicity may occur at concentrations within therapeutic range because potassium or magnesium depletion sensitizes the myocardium to digoxin. Therefore, it is desirable to maintain normal serum potassium and magnesium concentrations in patients being treated with digoxin. Serum potassium levels should be carefully monitored when digoxin is given to patients at high risk of hypokalemia (, those receiving diuretics, corticosteroids, or other drugs that commonly lead to potassium loss; those with gastrointestinal losses through diarrhea, vomiting, or nasogastric suction; or those with potassium-losing endocrinopathies or nephropathies). Digoxin toxicity is also more likely in the presence of hypomagnesemia. Hypomagnesemia is common in most of the same conditions in which hypokalemia appears. Most notably, it is commonly seen in alcoholics and in patients with diabetes mellitus or hypercalcemia. e.g.

Because digoxin’s therapeutic and toxic effects are all largely mediated by intracellular calcium distribution, they are affected by abnormalities in serum calcium levels. Hypercalcemia increases the risk of digoxin toxicity, while digoxin may be therapeutically ineffective in the presence of hypocalcemia.

5.7 Use in Electrical Cardioversion

Reduction of digoxin dosage may be desirable prior to electrical cardioversion to avoid induction of ventricular arrhythmias, but the physician must consider the consequences of a rapid increase in ventricular response to atrial fibrillation if digoxin is withheld 1 to 2 days prior to cardioversion. If there is a suspicion that digitalis toxicity exists, elective cardioversion should be delayed. If it is not prudent to delay cardioversion, the energy level selected should be minimal at first and carefully increased in an attempt to avoid precipitating ventricular arrhythmias.

5.8 Use in Thyroid Disorders and Hypermetabolic States

Hypothyrodism may reduce the requirements for digoxin. Heart failure and atrial arrhythmias resulting from hypermetabolic or hyperdynamic states (e.g., hyperthyroidism, hypoxia, or arteriovenous shunt) are best treated by addressing the underlying condition.

Atrial arrhythmias associated with hypermetabolic states (, hyperthyroidism) are particularly resistant to digoxin treatment. Large doses of digoxin are not recommended as the only treatment of these arrhythmias and care must be taken to avoid toxicity if large doses of digoxin are required. In hypothyroidism, the digoxin requirements are reduced. Digoxin responses are normal in patients with compensated thyroid disease. e.g.

5.9 Use in Patients with Acute Myocardial Infarction

In patients with acute myocardial infarction, particularly if they have ongoing ischemia, the use of inotropic drugs, such as digoxin, may result in undesirable increases in myocardial oxygen demand and ischemia. Moreover, the use of digoxin may result in potentially detrimental increases in coronary vascular resistance mediated through alpha adrenergic receptor stimulation.

5.10 Use in Patients with Myocarditis

Digoxin can precipitate vasoconstriction and may promote production of pro-inflammatory cytokines. Therefore, avoid digoxin in patients with myocarditis.

5.11 ECG Changes During Exercise

The use of therapeutic doses of digoxin may cause prolongation of the PR interval and depression of the ST segment on the electrocardiogram. Digoxin may produce false positive ST-T changes on the electrocardiogram during exercise testing that may be indistinguishable from those of ischemia. These electrophysiologic effects reflect an expected effect of the drug and are not indicative of toxicity. Digoxin does not significantly decrease heart rate during exercise.

5.12 Laboratory Tests

Patients receiving digoxin should have their serum electrolytes and renal function (serum creatinine concentrations) assessed periodically; the frequency of assessments will depend on the clinical setting.

Assays of serum digoxin levels are described elsewhere , as is their use in patient monitoring . [see ] Drug Interactions (7.4) [see Dosage and Administration (2.2)]

6 ADVERSE REACTIONS

The frequency and severity of adverse reactions to digoxin when taken orally depend on the dose and the patient's underlying disease or concomitant therapies The overall incidence of adverse reactions has been reported as 5 to 20%, with 15 to 20% of them being considered serious (1 to 4% of patients receiving digoxin). Evidence suggests that the incidence of toxicity has decreased since the introduction of the serum digoxin assay and improved standardization of digoxin tablets. Cardiac toxicity accounts for about one-half, gastrointestinal disturbances for about one-fourth, and CNS and other toxicity for about one-fourth of these adverse reactions. Adverse reactions are less common when digoxin is used within the recommended dose range or therapeutic serum concentration range and when there is careful attention to concurrent medications and conditions. [see and ] Warnings and Precautions (5) Drug Interactions (7).

6.1 Cardiac

In adults, high doses of digoxin may produce a variety of electrocardiographic changes and rhythm disturbances, such as first-degree, second-degree (Wenckebach), or third-degree heart block (including asystole); atrial tachycardia with block; AV dissociation; accelerated junctional (nodal) rhythm; unifocal or multifocal ventricular premature contractions (especially bigeminy or trigeminy); ventricular tachycardia; and ventricular fibrillation. Prophylactic use of a cardiac pacemaker may be considered if the risk of heart block is considered unacceptable.

In pediatric patients, the use of digoxin may produce arrhythmias. The most common are conduction disturbances or supraventricular tachycarrhythmias, such as atrial tachycardia (with or without block) and junctional (nodal) tachycardia. Ventricular arrhythmias are less common. Sinus bradycardia may be a sign of impending digoxin intoxication, especially in infants, even in the absence of first-degree heart block. Any arrhythmias or alteration in cardiac conduction that develops in a child taking digoxin should initially be assumed to be a consequence of digoxin intoxication.

6.2 Gastrointestinal

Anorexia, nausea, vomiting and diarrhea may be early symptoms of digoxin toxicity. However, uncontrolled heart failure may also produce such symptoms. The use of digoxin has been associated with abdominal pain, intestinal ischemia, and hemorrhagic necrosis of the intestines.

6.3 CNS and Special Senses

Digoxin can produce visual disturbances (blurred vision, green-yellow color disturbances, halo effect), headache, weakness, dizziness, apathy, confusion, and mental disturbances (such as anxiety, depression, delirium, and hallucination).

6.4 Other

Gynecomastia has been reported following the prolonged use of digoxin. Thrombocytopenia, maculopapular rash and other skin reactions have been observed.

7 DRUG INTERACTIONS

7.1 P-Glycoprotein (PGP) Inducers/Inhibitors

Digoxin is a substrate for P-glycoprotein, at the level of intestinal absorption, renal tubular section and biliary-intestinal secretion. Therefore, drugs that induce/inhibit P-glycoprotein have the potential to alter digoxin pharmacokinetics.

7.2 Pharmacokinetic Drug Interactions on Serum Digoxin Levels in Adults

Digoxin concentrations increased > 50%
 | Digoxin Serum Concentration Increase | Digoxin AUC Increase | Recommendations
Amiodarone | 70% | NA | Measure serum digoxin concentrations before initiating concomitant drugs. Reduce digoxin dose by approximately 30% to 50% and continue monitoring.
Captopril | 58% | 39% | Measure serum digoxin concentrations before initiating concomitant drugs. Reduce digoxin dose by approximately 30% to 50% and continue monitoring.
Nitrendipine | 57% | 15% | Measure serum digoxin concentrations before initiating concomitant drugs. Reduce digoxin dose by approximately 30% to 50% and continue monitoring.
Propafenone | 35-85% | NA | Measure serum digoxin concentrations before initiating concomitant drugs. Reduce digoxin dose by approximately 30% to 50% and continue monitoring.
Quinidine | 100% | NA | Measure serum digoxin concentrations before initiating concomitant drugs. Reduce digoxin dose by approximately 30% to 50% and continue monitoring.
Ranolazine | 87% | 88% | Measure serum digoxin concentrations before initiating concomitant drugs. Reduce digoxin dose by approximately 30% to 50% and continue monitoring.
Ritonavir | NA | 86% | Measure serum digoxin concentrations before initiating concomitant drugs. Reduce digoxin dose by approximately 30% to 50% and continue monitoring.
Verapamil | 50-75% | NA | Measure serum digoxin concentrations before initiating concomitant drugs. Reduce digoxin dose by approximately 30% to 50% and continue monitoring.
Digoxin concentrations increased < 50%
Carvedilol | 16% | 14% | Measure serum digoxin concentrations before initiating concomitant drugs. Reduce digoxin dose by approximately 15% to 30% and continue monitoring.
Diltiazem | 20% | NA | Measure serum digoxin concentrations before initiating concomitant drugs. Reduce digoxin dose by approximately 15% to 30% and continue monitoring.
Nifedipine | 45% | NA | Measure serum digoxin concentrations before initiating concomitant drugs. Reduce digoxin dose by approximately 15% to 30% and continue monitoring.
Rabeprazole | 29% | 19% | Measure serum digoxin concentrations before initiating concomitant drugs. Reduce digoxin dose by approximately 15% to 30% and continue monitoring.
Telmisartan | 20% | NA | Measure serum digoxin concentrations before initiating concomitant drugs. Reduce digoxin dose by approximately 15% to 30% and continue monitoring.
Digoxin concentrations increased, but magnitude is unclear
Alprazolam, Azithromycin, Clarithromycin, Cyclosporine, Diclofenac, Diphenoxylate, Epoprostenol, Erythromycin, Esomeprazole, Indomethacin, Itraconazole, Ketoconazole, Lansoprazole, Metformin, Omeprazole, Propantheline, Spironolactone, Tetracycline |  |  | Measure serum digoxin concentrations before initiating concomitant drugs. Continue monitoring and reduce digoxin dose as necessary.
Digoxin concentrations decreased
Acarbose, Activated Charcoal, Albuterol, Antacids, Anti-cancer drugs, Cholestyramine, Colestipol, Exenatide, Kaolin-pectin, Meals High in Bran, Metoclpramide, Miglitol, Neomycin, Rifampin, Salbutamol, St. John’s Wort, Sucralfate, Sulfasalazine |  |  | Measure serum digoxin concentrations before initiating concomitant drugs. Continue monitoring and increase digoxin dose by approximately 20% to 40% as necessary.
No significant Digoxin concentrations changes
Please refer to section 12.3 for a complete list of drugs which were studied but reported no significant changes on digoxin exposure. |  |  | No additional actions are required.

NA – Not available/reported

7.3 Pharmacodynamic Drug Interactions

Antiarrhythmics | Dofetilide | Concomitant administration with digoxin was associated with a higher rate of torsades de pointes.
Antiarrhythmics | Moricizine | Reported to increase PR interval and QRS duration. There are reports of first degree atrioventricular block or bundle branch block developing with digitalis administration. The known effects of moricizine on calcium conductance may explain the effects on atrioventricular node conduction.
Antiarrhythmics | Sotalol | Proarrhythmic events were more common in patients receiving sotalol and digoxin than on either alone; it is not clear whether this represents an interaction or is related to the presence of CHF, a known risk factor for proarrhythmia, in patients receiving digoxin.
Parathyroid Hormone Analog | Teriparatide | Sporadic case reports have suggested that hypercalcemia may predispose patients to digitalis toxicity. Teriparatide transiently increases serum calcium.
Thyroid Supplement | Thyroid | Treatment of hypothyroidism in patients taking digoxin may increase the dose requirements of digoxin.
Sympathomimetics | Epinepherine | Can increase the risk of cardiac arrhythmias.
Sympathomimetics | Norepinephrine | Can increase the risk of cardiac arrhythmias.
Sympathomimetics | Dopamine | Can increase the risk of cardiac arrhythmias.
Neuromuscular Blocking Agents | Succinylcholine | May cause sudden extrusion of potassium from muscle cells causing arrhythmias in patients taking digoxin.
Supplements | Calcium | If administered rapidly by intravenous route, can produce serious arrhythmias in digitalized patients.
Beta-adrenergic blockers and calcium channel blockers | Additive effects on AV node conduction can result in complete heart block.

7.4 Drug-Laboratory Test Interaction

Endogenous substances of unknown composition (digoxin-like immunoreactive substances, DLIS) can interfere with standard radioimmunoassays for digoxin. The interference most often causes results to be falsely positive or falsely elevated, but sometimes it causes results to be falsely reduced. Some assays are more subject to these failings than others. Several LC/MS/MS methods are available that may provide less susceptibility to DLIS interference. DLIS are present in up to half of all neonates and in varying percentages of pregnant women, patients with hypertrophic cardiomyopathy, patients with renal or hepatic dysfunction, and other patients who are volume-expanded for any reason. The measured levels of DLIS (as digoxin equivalents) are usually low (0.2 to 0.4 ng/mL), but sometimes they reach levels that would be considered therapeutic or even toxic.

In some assays, spironolactone, canrenone and potassium canrenoate may be falsely detected as digoxin, at levels up to 0.5 ng/mL. Some traditional Chinese and Ayurvedic medicine substances like Chan Su, Siberian Ginseng, Asian Ginseng, Ashwagandha or Dashen, can cause similar interference.

Spironolactone and DLIS are much more extensively protein-bound than digoxin. As a result, assays of free digoxin levels in protein-free ultrafiltrate (which tend to be about 25% less than total levels, consistent with the usual extent of protein binding) are less affected by spironolactone or DLIS. It should be noted that ultrafiltration does not solve all interference problems with alternative medicines. The use of an LC/MS/MS method may be the better option according to the good results it provides, especially in term of specificity and limit of quantization.

8 USE IN SPECIFIC POPULATIONS

8.1 Pregnancy

Teratogenic Effects (Pregnancy Category C)

Animal reproduction studies have not been conducted with digoxin. It is also not known whether digoxin can cause fetal harm when administered to pregnant women or can affect reproductive capacity. Digoxin should be given to a pregnant woman only if clearly needed.

8.2 Labor and Delivery

There is not enough data from clinical trials to determine the safety and efficacy of digoxin during labor and delivery.

8.3 Nursing Mothers

Digoxin levels in human milk are lower than those in maternal serum. The estimated exposure that a nursing infant would be expected to receive via breastfeeding would be far below the usual infant maintenance dose. Therefore, this amount should have no pharmacologic effect upon the infant. Nevertheless, caution should be exercised when digoxin is administered to a nursing woman.

8.4 Pediatric Use

Digoxin increases myocardial contractility in pediatric patients with congestive heart failure. There are no clinical efficacy studies demonstrating benefit in pediatric patients with heart failure. There are no controlled randomized studies of digoxin in pediatric patients with atrial tachyarrhythmias . [see ] Clinical Studies (14.2)

8.5 Geriatric Use

The majority of clinical experience gained with digoxin has been in the elderly population. This experience has not identified differences in response or adverse effects between the elderly and younger patients. However, this drug is known to be substantially excreted by the kidney, and the risk of toxic reactions to this drug may be greater in patients with impaired renal function. Because elderly patients are more likely to have decreased renal function, care should be taken in dose selection, which should be based on renal function, and it may be useful to monitor renal function [see ] Dosage and Administration (2.4).

8.6 Gender

No clinically significant gender differences in digoxin pharmacokinetics have been reported.

8.7 Renal Impairment

The clearance of digoxin can be primarily correlated with renal function as indicated by creatinine clearance. Table 3 provides the usual daily maintenance dose requirements of solution based on creatinine clearance (per 70 kg or per 1.73 m) ].^2 [see Dosage and Administration (2.4)

For pediatric patients with known or suspected renal dysfunction, lower starting doses should be considered combined with frequent monitoring of digoxin levels.

8.8 Hepatic Impairment

Plasma digoxin concentrations in patients with acute hepatitis generally fall within the range of profiles in a group of healthy subjects.

8.9 Thyroid Status

In hyperthyroidism, lower serum digoxin concentrations have been reported because of decreased absorption. Hypothyroid patients may require smaller doses of digoxin.

8.10 Race

Race differences in digoxin pharmacokinetics have not been formally studied, but are not expected.

8.11 Malabsorption Conditions

Race differences in digoxin pharmacokinetics have not been formally studied, but are not expected.

10 OVERDOSAGE

10.1 Clinical Manifestations

In adults, the signs and symptoms of toxicity are similar to those described in but may be more frequent and severe. The most common signs and symptoms of digoxin toxicity are nausea, vomiting, anorexia, and fatigue that occur in 30 to 70% of patients who are overdosed. Extremely high serum concentrations produce hyperkalemia especially in patients with impaired renal function. Almost every type of cardiac arrhythmia has been associated with digoxin overdose and multiple rhythm disturbances in the same patient are common. Peak cardiac effects occur 3 to 6 hours following ingestion and may persist for 24 hours or longer. Arrhythmias that are considered more characteristic of digoxin toxicity are new-onset Mobitz type 1 A-V block, accelerated junctional rhythms, non-paroxysmal atrial tachycardia with A-V block, and bi-directional ventricular tachycardia. Cardiac arrest from asystole or ventricular fibrillation is usually fatal. Adverse Reactions (6)

Digoxin toxicity is related to serum concentration. As serum levels increase above 1.2 ng/mL, there is a potential for increase in adverse events. The effect on adverse events is enhanced by lower potassium levels. In adults with heart disease, clinical observations suggest that an overdose of digoxin of 10 to 15 mg results in death of half of patients. A dose above 25 mg ingested by an adult without heart disease appeared to be uniformly fatal if no Digoxin Immune Fab (DIGIBIND®, DIGIFAB®) was administered.

In pediatric patients, signs and symptoms of toxicity can occur during or shortly after the dose of digoxin. Frequent non-cardiac effects are similar to those observed in adults although nausea and vomiting are not seen frequently in infants and small pediatric patients. Other reported manifestations of overdose are weight loss in older age groups, failure to thrive in infants, abdominal pain caused by mesenteric artery ischemia, drowsiness, and behavioral disturbances including psychotic episodes. Arrhythmias and combinations of arrhythmias that occur in adult patients can also occur in pediatric patients although sinus tachycardia, supraventricular tachycardia, and rapid atrial fibrillation are seen less frequently in pediatric patients. Pediatric patients are more likely to develop A-V conduction disturbances, or sinus bradycardia. Any arrhythmia in a child treated with digoxin should be considered related to digoxin until otherwise ruled out. In pediatric patients aged 1 to 3 years without heart disease, clinical observations suggest that an overdose of digoxin of 6 to 10 mg would result in death of half of the patients. In the same population, a dose above 10 mg resulted in death if no Digoxin Immune Fab (DIGIBIND®, DIGIFAB®) was administered.

10.2 Management of Toxicity

Chronic Overdose

If there is suspicion of toxicity, digoxin should be discontinued and the patient placed on a cardiac monitor. Contributing factors such as electrolyte abnormalities, thyroid dysfunction, and concomitant medications should be corrected Hypokalemia should be corrected by administering potassium so that serum potassium is maintained between 4.0 and 5.5 mmol/L. Potassium is usually administered orally, but when correction of the arrhythmia is urgent and serum potassium concentration is low, potassium may be administered cautiously by the intravenous route. The electrocardiogram should be monitored for any evidence of potassium toxicity (e.g. peaking of T waves) and to observe the effect on the arrhythmia. Potassium salts should be avoided in patients with bradycardia or heart block. Symptomatic arrhythmias may be treated with Digoxin Immune Fab (DIGIBIND®, DIGIFAB®). [see . ] Dosage and Administration (2.5)

Acute Overdose

Patients who have intentionally or accidently ingested massive doses of digoxin should receive activated charcoal orally or by nasogastric tube regardless of the time since ingestion since digoxin recirculates to the intestine by enterohepatic circulation. In addition to cardiac monitoring, digoxin should be temporarily discontinued until the adverse reaction resolves. Factors that may be contributing to the adverse reactions should also be corrected . In particular, hypokalemia and hypomagnesemia should be corrected. Digoxin is not effectively removed from the body by dialysis because of its large extravascular volume of distribution. Life threatening arrhythmias (ventricular tachycardia, ventricular fibrillation, high degree A-V block, bradyarrhythma, sinus arrest) or hyperkalemia requires administration of Digoxin Immune Fab (DIGIBIND , DIGIFAB). Digoxin Immune Fab has been shown to be 80-90% effective in reversing signs and symptoms of digoxin toxicity. Bradycardia and heart block caused by digoxin are parasympathetically mediated and respond to atropine. A temporary cardiac pacemaker may also be used. Ventricular arrhythmias may respond to lidocaine or phenytoin. When a large amount of digoxin has been ingested, especially in patients with impaired renal function, hyperkalemia may be present due to release of potassium from skeletal muscle. In this case, treatment with Digoxin Immune Fab (DIGIBIND , DIGIFAB) is indicated; an initial treatment with glucose and insulin may be needed if the hyperkalemia is life-threatening. Once the adverse reaction has resolved, therapy with digoxin may be reinstituted following a careful reassessment of dose. [see] Warnings and Precautions (5)®®®®

11 DESCRIPTION

Digoxin is one of the cardiac glycosides, a closely-related group of plant-derived drugs with shared pharmacological effects. The term "digitalis" is used to designate the whole group. Digoxin is extracted from the leaves of the common foxglove, . Like each of the other cardiac glycosides, digoxin consists of a polycyclic core and a sugar side chain. Digoxin’s chemical name is 3β-[ -2,6-dideoxy-β-D- -hexopyranosyl-(1→4)- -2, 6-dideoxy-β-D- -hexopyranosyl-(1→4)-2, 6-dideoxy-β-D- -hexopyranosyl)oxy]-12β, 14-dihydroxy-5β-card-20(22)-enolide; its structural formula is: Digitalis lanata 0 ribo 0 riboribo

Its molecular formula is C H O , and its molecular weight is 780.95. Digoxin is practically insoluble in water and in ether, slightly soluble in 50% ethanol and in chloroform, and freely soluble in pyridine. Digoxin powder consists of odorless white crystals.416414

Digoxin Oral Solution, USP is formulated for oral administration, and each mL contains 50 mcg (0.05 mg digoxin). The lime-flavored solution contains the following inactive ingredients: alcohol 10% (by volume at 60°F), glycerin, lime (imitation), methylparaben 0.1%, propylparaben 0.02%, purified water, sodium citrate, and sorbitol solution.

12 CLINICAL PHARMACOLOGY

12.1 Mechanism of Action

All of digoxin’s actions are mediated through its effects on NaK–ATPase. This enzyme, the “sodium pump,” is responsible for maintaining the intracellular milieu throughout the body by moving sodium ions out of and potassium ions into cells. By inhibiting NaK–ATPase, digoxin

- causes increased availability of intracellular calcium in the myocardium and conduction system, with consequent increased inotropy, increased automaticity, and reduced conduction velocity;
- indirectly causes parasympathetic stimulation of the autonomic nervous system, with consequent effects on the sino-atrial (SA) and atrioventricular (AV) nodes;
- reduces catecholamine reuptake at nerve terminals, rendering blood vessels more sensitive to endogenous or exogenous catecholamines;
- increases baroreceptor sensitization, with consequent increased carotid sinus nerve activity and enhanced sympathetic withdrawal for any given increment in mean arterial pressure;
- increases (at higher concentrations) sympathetic outflow from the central nervous system (CNS) to both cardiac and peripheral sympathetic nerves; and
- allows (at higher concentrations) progressive efflux of intracellular potassium, with consequent increase in serum potassium levels.

The cardiologic consequences of these direct and indirect effects are an increase in the force and velocity of myocardial systolic contraction (positive inotropic action), a slowing of the heart rate (negative chronotropic effect), and decreased conduction velocity through the AV node, and a decrease in the degree of activation of the sympathetic nervous system and renin-angiotensin system (neurohormonal deactivating effect).

12.2 Pharmacodynamics

Short- and long-term treatment with digoxin slows heart rate, increases cardiac output and lowers pulmonary artery pressure, pulmonary capillary wedge pressure, and systemic vascular resistance. These hemodynamic effects are accompanied by an increase in the left ventricular ejection fraction and a decrease in end-systolic and end-diastolic dimensions.

12.3 Pharmacokinetics

Absorption

Following oral administration, peak serum concentrations of digoxin occur at 30 to 90 minutes. In pediatric patients and in adult volunteers, absolute bioavailability of digoxin from the solution formulation is 70 to 85%, similar to that seen (in adults) with standard tablets (60 to 80%). When the solution is taken after meals, the peak serum concentrations increase by 20% and the total amount of digoxin absorbed increases by 43%, but the rate of digoxin absorption is unchanged. When taken with meals high in bran fiber, however, the amount absorbed from an oral dose may be reduced. Digoxin absorption may also be affected by various concomitant therapy modulating gastric pH and P-glycoprotein . [see ] Drug Interactions (7)

Comparisons of the systemic availability and equivalent doses for preparations of digoxin are shown in . Table 5

Table 5: Comparisons of the Systemic Availability and Equivalent Doses for Preparations of Digoxin
Product | Absolute Bioavailability | Equivalent Doses (mcg) Among Dosage Forms [For example, 125 mcg tablets equivalent to 125 mcg solution equivalent to 100 mcg capsules equivalent to 100 mcg injection/IV.]
Tablets | 60-80% | 62.5 | 125 | 250 | 500
Solution | 70-85% | 62.5 | 125 | 250 | 500
Capsules | 90-100% | 50 | 100 | 200 | 400
Injection/IV | 100% | 50 | 100 | 200 | 400

In some patients, orally administered digoxin is converted to inactive reduction products (e.g., dihydrodigoxin) by colonic bacteria in the gut. Data suggested that one in ten patients treated with digoxin will degrade 40% or more of the ingested dose. As a result, certain antibiotics may increase the absorption of digoxin in such patients. The magnitude of rise in serum digoxin concentration relates to the extent of bacterial inactivation, and may be as much as two-fold in some cases.

Distribution

Following drug administration, a 6- to 8-hour tissue distribution phase is observed. This is followed by a much more gradual decline in the serum concentration of the drug, which is dependent on the elimination of digoxin from the body. Clinical evidence indicates that the early high serum concentrations do not reflect the concentration of digoxin at its sites of action, but that with chronic use, the steady-state post-distribution serum concentrations are in equilibrium with tissue concentrations and correlate with pharmacologic effects. In individual patients, these post-distribution serum concentrations may be useful in evaluating therapeutic and toxic effects . [see ] Dosage and Administration (2.2)

Digoxin is concentrated in tissues and therefore has a large apparent volume of distribution. Digoxin crosses both the blood-brain barrier and the placenta. At delivery, the serum digoxin concentration in the newborn is similar to the serum concentration in the mother. Approximately 25% of digoxin in the plasma is bound to protein. Serum digoxin concentrations are not significantly altered by large changes in fat tissue weight, so that its distribution space correlates with lean (i.e., ideal) body weight, not total body weight.

Metabolism

Sixteen percent of digoxin is metabolized. The end metabolites include 3-β-digoxigenin, 3-keto-digoxigenin, and their glucuronide and sulfate conjugates. The metabolism of digoxin is not dependent on the cytochrome P-450 system, and digoxin is not known to induce or inhibit the cytochrome P-450 system.

Excretion

Elimination of digoxin is predominantly renal, although in adult volunteers about a quarter of serum digoxin is eliminated through the intestine, excreted in bile or secreted directly into the lumen by P-glycoprotein. Elimination of digoxin follows first order kinetics.

Following intravenous administration to healthy volunteers, 50% to 70% of a digoxin dose is excreted unchanged in the urine. Renal excretion of digoxin is proportional to glomerular filtration rate.

The serum half-life of digoxin in pediatric patients is reported to be 18 to 36 hours, and in adults it is typically 36 to 48 hours. The half-life in anuric patients is prolonged to 3.5 to 5 days.

Digoxin is not effectively removed from the body by dialysis, exchange transfusion, or cardiopulmonary bypass because most of the drug is bound to tissue.

Drug-drug Interactions

Based on literature reports no significant changes in digoxin exposure were reported when digoxin was co-administered with the following drugs: alfuzosin, aliskiren, amlodipine, aprepitant, argatroban, aspirin, atorvastatin, benazepril, bisoprolol, black cohosh, bosentan, candesartan, citalopram, clopidogrel, colesevelam, dipyridamole, disopyramide, donepezil, doxazosin, dutasteride, echinacea, enalapril, eprosartan, ertapenem, escitalopram, esmolol, ezetimibe, famciclovir, felodipine, finasteride, flecainide, fluvastatin, fondaparinux, galantamine, gemifloxacin, grapefruit juice, irbesartan, isradipine, ketorolac, levetiracetam, levofloxacin, lisinopril, losartan, lovastatin, meloxicam, mexilitine, midazolam, milk thistle, moexipril, montelukast, moxifloxacin, mycophenolate, nateglinide, nesiritide, nicardipine, nisoldipine, olmesartan, orlistat, pantoprazole, paroxetine, perindopril, pioglitazone, pravastatin, prazosin, procainamide, quinapril, raloxifene, ramipril, repaglinide, rivastigmine, rofecoxib, ropinirole, rosiglitazone, rosuvastatin, sertraline, sevelamer, simvastatin, sirolimus, solifenacin, tamsulosin, tegaserod, terbinafine, tiagabine, ticlopidine, tigecycline, topiramate, torsemide, tramadol, trandolapril, triamterene, trospium, trovafloxacin, valacyclovir, valsartan, varenicline, voriconazole, zaleplon, and zolpidem.

13 NONCLINICAL TOXICOLOGY

13.1 Carcinogenesis, Mutagenesis, Impairment of Fertility

There have been no long-term studies performed in animals to evaluate carcinogenic potential, nor have studies been conducted to assess the mutagenic potential of digoxin or its potential to affect fertility.

14 CLINICAL STUDIES

14.1 Chronic Heart Failure

Two small12-week, double-blind, randomized trials compared digoxin to placebo in adult patients with chronic congestive heart failure, New York Heart Association Class II or III. The enrolled patients had all been receiving digoxin before the trials, but this was withdrawn before randomization. They continued to receive diuretics and (in the larger trial) ACE inhibitors. The trials enrolled 178 and 88 patients, respectively. In each of these trials, randomization to digoxin was associated with better preservation of exercise capacity and with reduced need of failure-related hospitalization, emergency care, and concomitant heart-failure therapy. NYHA class and patients' global assessments were also improved, although this effect achieved statistical significance only in the larger of the two studies.

The Digitalis Investigation Group (DIG) main trial was a 37-week, multicenter, randomized, double-blind mortality study comparing digoxin to placebo in 6800 adult patients with heart failure and left ventricular ejection fraction ≤0.45. At randomization, 67% were NYHA class I or II, 71% had heart failure of ischemic etiology, 44% had been receiving digoxin, and most were receiving a concomitant ACE inhibitor (94%) and diuretics (82%). As in the smaller trials described above, patients who had been receiving open-label digoxin were withdrawn from this treatment before randomization. Randomization to digoxin was again associated with a significant reduction in the incidence of hospitalization, whether scored as number of hospitalizations for heart failure (relative risk 75%), risk of having at least one such hospitalization during the trial (RR 72%), or number of hospitalizations for any cause (RR 94%). On the other hand, randomization to digoxin had no apparent effect on mortality (RR 99%, with confidence limits of 91 to 107%).

14.2 Atrial Fibrillation

Digoxin has also been studied as a means of controlling the ventricular response to chronic atrial fibrillation in adults. Digoxin reduced the resting heart rate, but not the heart rate during exercise.

In 3 different randomized, double-blind trials that included a total of 315 adult patients, digoxin was compared to placebo for the conversion of recent-onset atrial fibrillation to sinus rhythm. Conversion was equally likely, and equally rapid, in the digoxin and placebo groups. In a randomized 120-patient trial comparing digoxin, sotalol, and amiodarone, patients randomized to digoxin had the lowest incidence of conversion to sinus rhythm, and the least satisfactory rate control when conversion did not occur.

In at least one study, digoxin was studied as a means of delaying reversion to atrial fibrillation in adult patients with frequent recurrence of this arrhythmia. This was a randomized, double-blind, 43-patient crossover study. Digoxin increased the mean time between symptomatic recurrent episodes by 54%, but had no effect on the frequency of fibrillatory episodes seen during continuous electrocardiographic monitoring.

No controlled randomized study of digoxin in pediatric patients with atrial tachyarrhythmias has been done.

14.3 Atrial Flutter

There are no reports of controlled trials of digoxin for conversion of atrial flutter, rate control during atrial flutter, or reduction of the frequency of recurrence of atrial flutter in adults.

14.4 Supraventricular Tachycardia

There are no reports of controlled trials of digoxin for conversion of supraventricular tachycardia (SVT), rate control during SVT, or reduction of the frequency of recurrence of SVT in adults.

17 PATIENT COUNSELING INFORMATION

Patients receiving digoxin should be given the following instructions by the physician.

- Advise patients that digoxin is a cardiac glycoside used to treat heart failure and heart arrhythmias. Digoxin helps the heart beat more efficiently in adults and pediatric patients and decreases the heart rate at rest during abnormal rhythms in adults.
- Instruct patients to take this medication as directed by their physician. The dose of digoxin should not be adjusted without consulting with a physician or other healthcare professional.
- Advise patients that many drugs can interact with digoxin. Patients should be instructed to inform their doctor and pharmacist if they are taking any over the counter medications, including herbal medication, or are started on a new prescription.
- The patient should be made aware that blood tests will be necessary to ensure that their digoxin dose is appropriate for them.
- Advise patients to contact their doctor or a health care professional if they experience nausea, vomiting, persistent diarrhea, confusion, weakness, or visual disturbances (including blurred vision, green-yellow color disturbances, halo effect) as these could be signs that the dose of digoxin may be too high.
- Advise parents or caregivers that the symptoms of having too high digoxin doses may be difficult to recognize in infants and pediatric patients. Symptoms such as weight loss, failure to thrive in infants, abdominal pain, and behavioral disturbances may be indications of digoxin toxicity.
- Suggest to the patient to monitor and record their heart rate and blood pressure daily.
- Instruct patients to use the calibrated dropper to measure their digoxin dose and to avoid less precise measuring tools, such as teaspoons. For doses less than 0.2 mL, another measuring syringe should be provided to the patient for accurate dosing, since the provided calibrated dropper is not appropriate to measure doses less than 0.2 mL.
- Instruct women of childbearing potential who become or are planning to become pregnant to consult a physician prior to initiation or continuing therapy with digoxin.